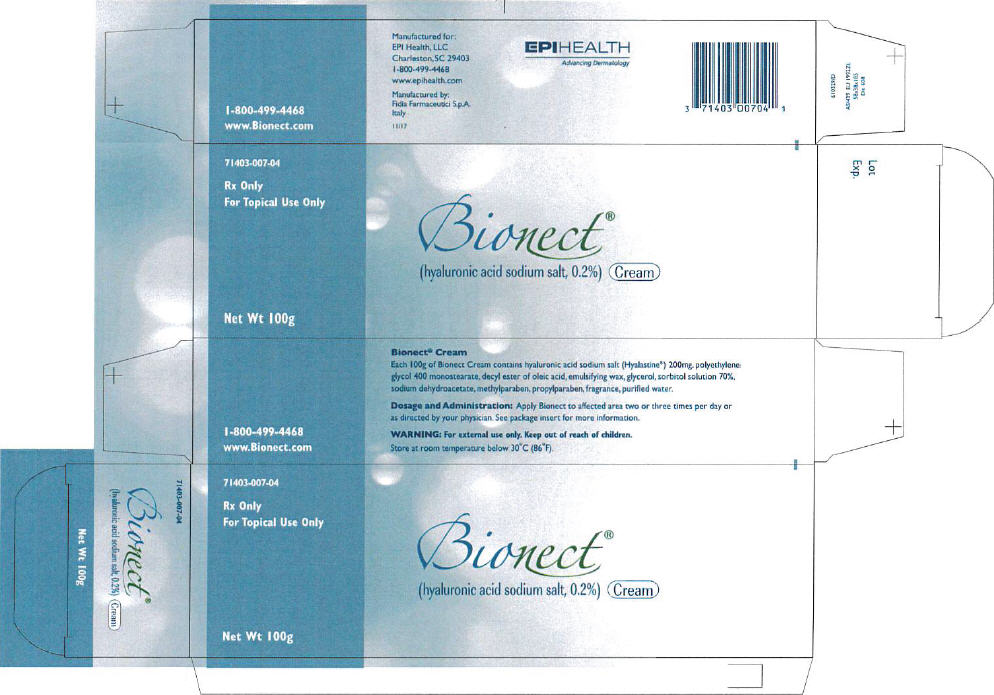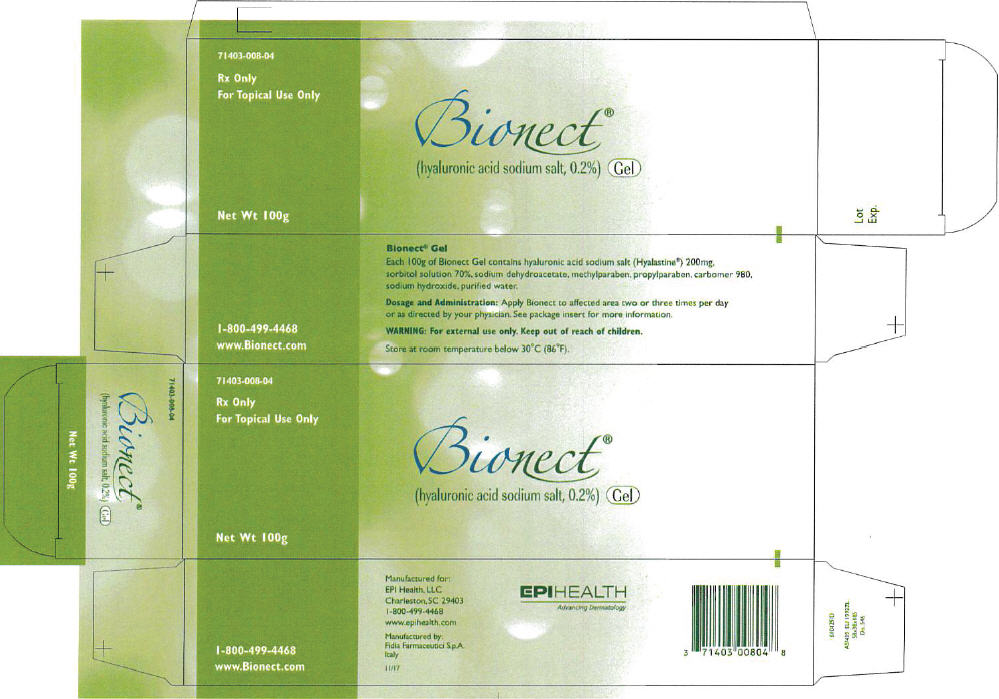 DRUG LABEL: Bionect
NDC: 71403-007
Manufacturer: EPI Health, Inc
Category: other | Type: PRESCRIPTION MEDICAL DEVICE LABEL
Date: 20180309

ACTIVE INGREDIENTS: Hyaluronate sodium 0.2 g/1 g
INACTIVE INGREDIENTS: polyethylene glycol, unspecified; decyl oleate; white wax; glycerin; sorbitol; sodium dehydroacetate; methylparaben; propylparaben; Water

BIONECT® Cream
BIONECT® Gel

For topical use only. Rx only.

Product Description

BIONECT Cream is a white, viscous cream. BIONECT Gel is a clear, colorless gel. The principal component is the sodium salt of hyaluronic acid (0.2%). The sodium hyaluronate (Hyalastine®) is derived from a natural fermentation process. Hyaluronic acid is a biological polysaccharide (glycosaminoglycan) and is a major component of the extracellular matrix of connective tissues.

Indications

BIONECT is indicated for the dressing and management of partial to full thickness dermal ulcers (pressure sores, venous stasis ulcers, arterial ulcers, diabetic ulcers), wounds including cuts, abrasions, donor sites, and post-operative incisions, irritations of the skin, and first and second degree burns. The dressing is intended to cover a wound or burn on a patient's skin, and protect against abrasion, friction, and desiccation.

Directions

The wounds or ulcers should be cleaned and disinfected prior to treatment. In the event of long-standing ulcers, it may be advisable to clean and/or to debride the wound by surgical or enzymatic means, prior to treatment. Apply a thin layer of BIONECT without extensive rubbing onto the wound surface, two or three times per day. Cover the lesion area with a sterile gauze pad and, if necessary, with an elastic or compressive bandage.

Warnings

If condition worsens, consult your physician immediately. Keep this product out of the reach of children. The prolonged use of the product may give rise to sensitization phenomena. Should this happen, discontinue the treatment and follow a suitable therapy. Do not use the product after the expiration date reported on the package or if the package is damaged.

Ingredients

BIONECT Cream

Hyaluronic acid sodium salt, polyethylene glycol 400 monostearate, decyl ester of oleic acid, emulsifying wax, glycerol, sorbitol solution 70%, sodium dehydroacetate, methylparaben, propylparaben, fragrance, purified water.

BIONECT Gel

Hyaluronic acid sodium salt, sorbitol solution 70%, sodium dehydroacetate, methylparaben, propylparaben, carbomer 980, sodium hydroxide, purified water.

Contraindications

Do not administer to patients with known hypersensitivity to this product.

Interactions

Do not use concomitantly with disinfectants containing quaternary ammonium salts because hyaluronic acid can precipitate in their presence. The concomitant topical treatment of wounds with antibiotics or other local agents has never given rise to interactions or incompatibilities with BIONECT.

Precautions

Avoid direct contact of container with the affected area. Each container of BIONECT should be used by one patient only in order to reduce the risk of cross infection.

WARNING

Keep out of reach of children.

Adverse Reactions

All suspected adverse reactions occurring during the treatment with BIONECT should be reported to your doctor.

How Supplied

BIONECT Cream/Gel is supplied in a:

25g Cream - 71403-007-02
100g Cream - 71403-007-04
100g Gel - 71403-008-04

Storage

BIONECT Cream may be stored for up to 24 months, BIONECT Gel may be stored for up to 24 months. Store at room temperature below 86°F (30°C).

Manufactured by: Fidia Farmaceutici S.p.A. - Italy

Distributed by: EPI Health, LLC
Charleston, SC 29403
1-800-499-4468
www.epihealth.com
www.Bionect.com

November 2017

Bionect and Hyalastine are registered trademarks of Fidia Farmaceutici S.p.A.

610386/H

PRINCIPAL DISPLAY PANEL - 100 g Tube Carton - Cream

71403-007-04

Rx Only
For Topical Use Only

Bionect®
(hyaluronic acid sodium salt, 0.2%) Cream

Net Wt 100g

PRINCIPAL DISPLAY PANEL - 100 g Tube Carton - Gel

71403-008-04

Rx Only
For Topical Use Only

Bionect®
(hyaluronic acid sodium salt, 0.2%) Gel

Net Wt 100g